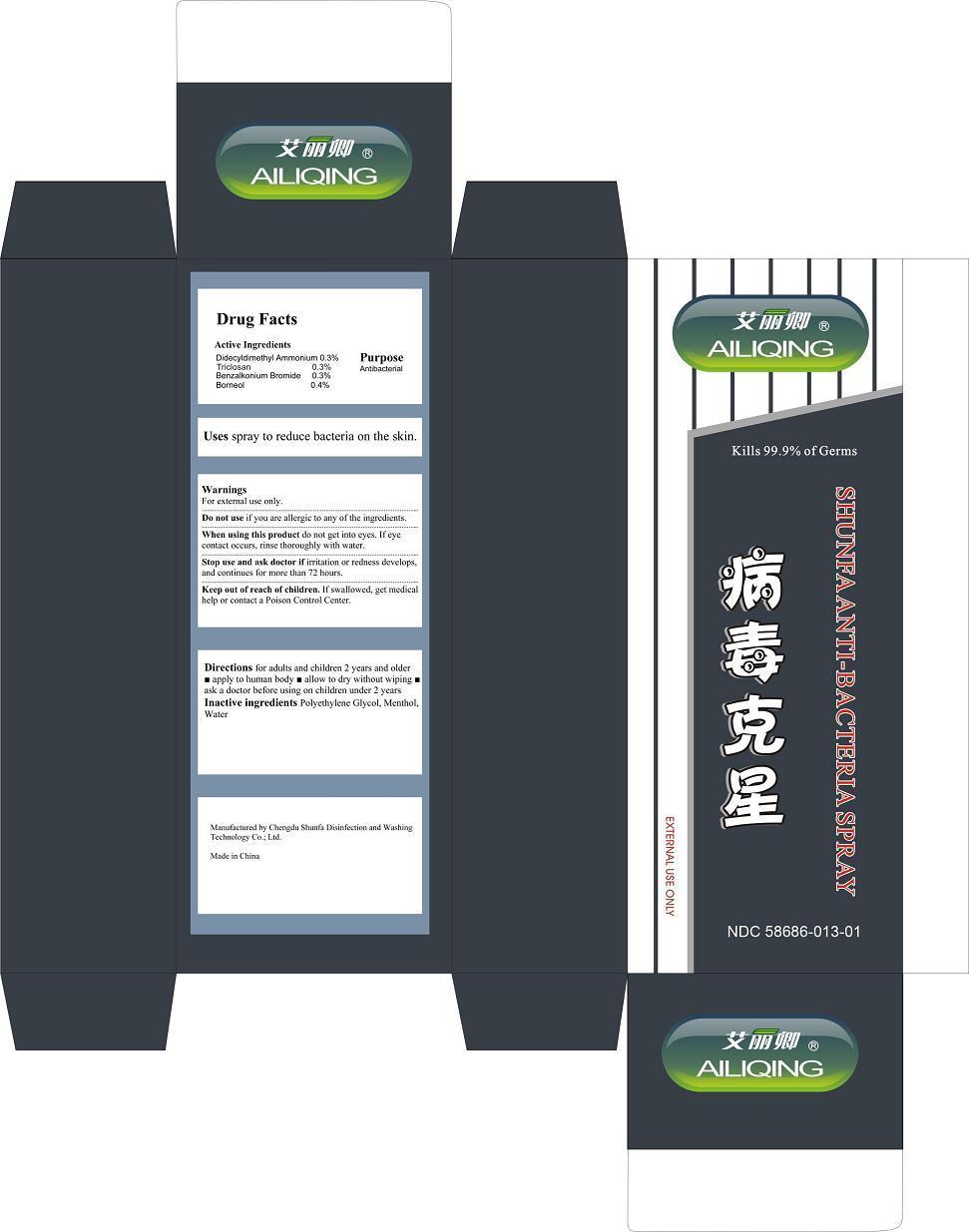 DRUG LABEL: Shunfa Anti-Bacteria Spra
NDC: 58686-013 | Form: SPRAY
Manufacturer: Chengdu Shunfa Disinfection and Washing Technology Co Ltd
Category: otc | Type: HUMAN OTC DRUG LABEL
Date: 20130605

ACTIVE INGREDIENTS: DIDECYLDIMETHYLAMMONIUM 3 mg/1000 mg; TRICLOSAN 3 mg/1000 mg; BENZALKONIUM BROMIDE 3 mg/1000 mg; BORNEOL 4 mg/1000 mg
INACTIVE INGREDIENTS: POLYETHYLENE GLYCOL 1000 100 mg/1000 mg; MENTHOL 3 mg/1000 mg; WATER 800 mg/1000 mg

SHUNFA ANTI-BACTERIA SPRAY

ACTIVE INGREDIENTS

Didecyldimethyl Ammonium 0.3%

Triclosan 0.3%

Borneol 0.4%

Benzalkonium Bromide 0.3%

PURPOSES

Antibacterial

KEEP OUT OF REACH OF CHILDREN.

If swallowed, get medical help or contact a Poison Control Center.

DO NOT USE

if you are allergic to any of the ingredients.

WHEN USING THIS DEVICE

do not get into eyes. If eye contact occurs, rinse thoroughly with water.

STOP USE AND ASK A DOCTOR IF

irritation or redness develops, and continues for more than 72 hours.

USES

Uses spray to reduce bacteria on the skin.

WARNINGS

For external use only.

DIRECTIONS

for adults and children 2 years and olde, apply to human body, allow to dry without wiping, ask a doctor before using on children under 2 years.

INACTIVE INGREDIENTS

Polyethylene Glycol, Menthol, Water